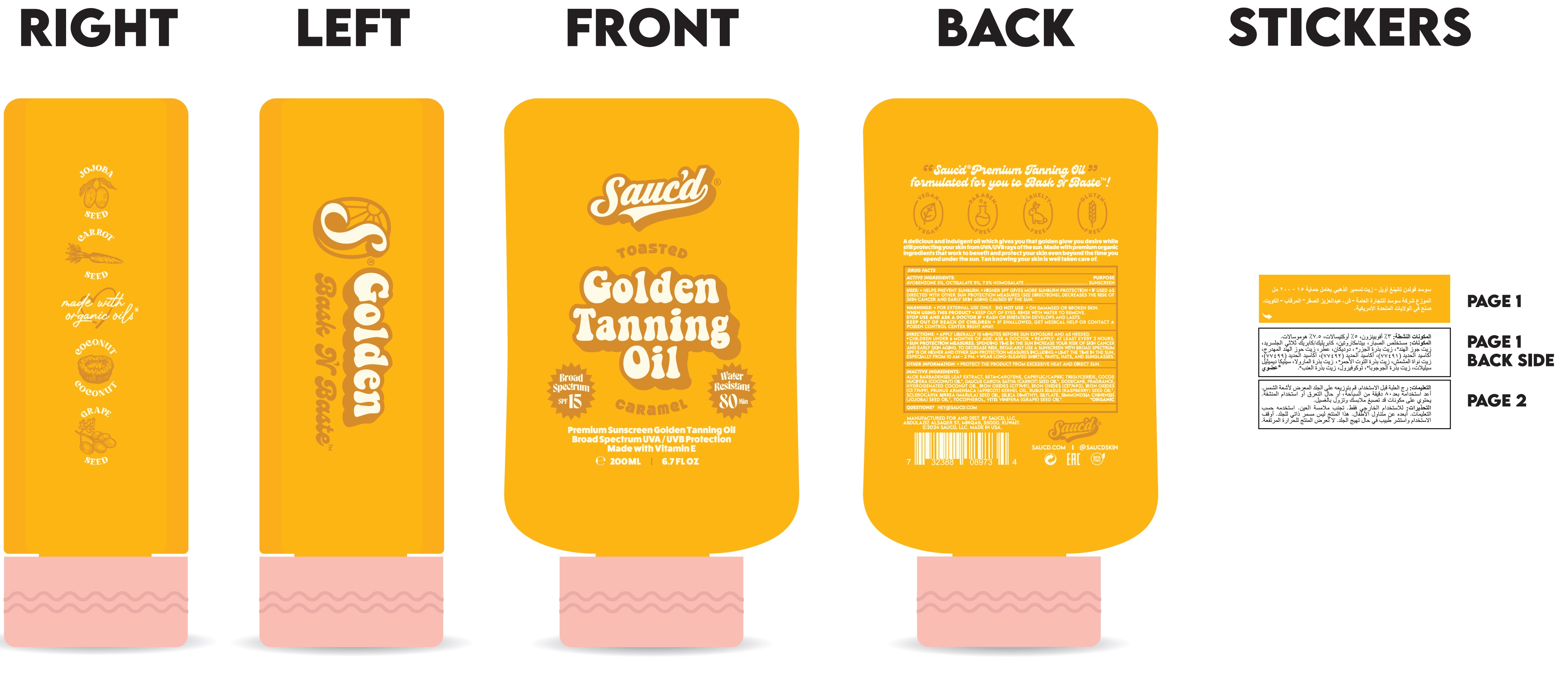 DRUG LABEL: Saucd Toasted Golden Tanning SPF 15 Caramel
NDC: 85618-596 | Form: OIL
Manufacturer: SAUCD GENERAL TRADING COMPANY
Category: otc | Type: HUMAN OTC DRUG LABEL
Date: 20250505

ACTIVE INGREDIENTS: AVOBENZONE 30 mg/1 mL; OCTISALATE 50 mg/1 mL; HOMOSALATE 75 mg/1 mL
INACTIVE INGREDIENTS: ALOE VERA LEAF; BETA CAROTENE; MEDIUM-CHAIN TRIGLYCERIDES; COCONUT OIL; CARROT SEED OIL; DODECANE; HYDROGENATED COCONUT OIL; FERRIC OXIDE RED; FERRIC OXIDE YELLOW; FERROSOFERRIC OXIDE; APRICOT KERNEL OIL; RASPBERRY SEED OIL; SILICA DIMETHYL SILYLATE; JOJOBA OIL; TOCOPHEROL; GRAPE SEED OIL

Sauc'd Toasted Golden Tanning Oil SPF 15, Caramel

ACTIVE INGREDIENTS:

AVOBENZONE 3%

OCTISALATE 5%

7.5% HOMOSALATE

PURPOSE

SUNSCREEN

USES:

• HELPS PREVENT SUNBURN.
• HIGHER SPF GIVES MORE SUNBURN PROTECTION
• IF USED AS DIRECTED WITH OTHER SUN PROTECTION MEASURES (SEE DIRECTIONS), DECREASES THE RISK OF SKIN CANCER AND EARLY SKIN AGING CAUSED BY THE SUN.

WARNINGS:

- FOR EXTERNAL USE ONLY

DO NOT USE

• ON DAMAGED OR BROKEN SKIN.

WHEN USING THIS PRODUCT

- KEEP OUT OF EYES. RINSE WITH WATER TO REMOVE.

STOP USE AND ASK A DOCTOR IF

- RASH OR IRRITATION DEVELOPS AND LASTS.

KEEP OUT OF REACH OF CHILDREN.

IF SWALLOWED, GET MEDICAL HELP OR CONTACT A POISON CONTROL CENTER RIGHT AWAY.

DIRECTIONS:

- APPLY LIBERALLY 15 MINUTES BEFORE SUN EXPOSURE AND AS NEEDED.
- CHILDREN UNDER 6 MONTHS OF AGE: ASK A DOCTOR.
- REAPPLY: AT LEAST EVERY 2 HOURS
- SUN PROTECTION MEASURES.SPENDING TIME IN THE SUN INCREASE YOUR RISK OF SKIN CANCER AND EARLY SKIN AGING. TO DECREASE RISK, REGULARLY USE A SUNSCREEN WITH A BROAD SPECTRUM SPF OF 15 OR HIGHER AND OTHER SUN PROTECTION MEASURES INCLUDING:
  • LIMIT TIME IN THE SUN, ESPECIALLY FROM 10 A.M.-2P.M.
  • WEAR LONG-SLEEVED SHIRTS, PANTS, HATS, AND SUNGLASSES.

OTHER INFORMATION

• PROTECT THE PRODUCT FROM EXCESSIVE HEAT AND DIRECT SUN.

INACTIVE INGREDIENTS:

ALOE BARBADENSIS LEAF EXTRACT, BETA-CAROTENE, CAPRYLIC/CAPRIC TRIGLYCERIDE, COCOS NUCIFERA (COCONUT) OIL*, DAUCUS CAROTA SATIVA (CARROT) SEED OIL*, DODECANE, FRAGRANCE, HYDROGENATED COCONUT OIL, IRON OXIDES (CI77491), IRON OXIDES (CI77492), IRON OXIDES (CI 77499), PRUNUS ARMENIACA (APRICOT) KERNEL OIL, RUBUS IDAEUS (RASPBERRY) SEED OIL*, SCLEROCARYA BIRREA (MARULA) SEED OIL, SILICA DIMETHYL SILYLATE, SIMMONDSIA CHINENSIS (JOJOBA) SEED OIL*, TOCOPHEROL, VITIS VINIFERA (GRAPE) SEED OIL*. *ORGANIC

QUESTIONS?

HEY@SAUCD.COM